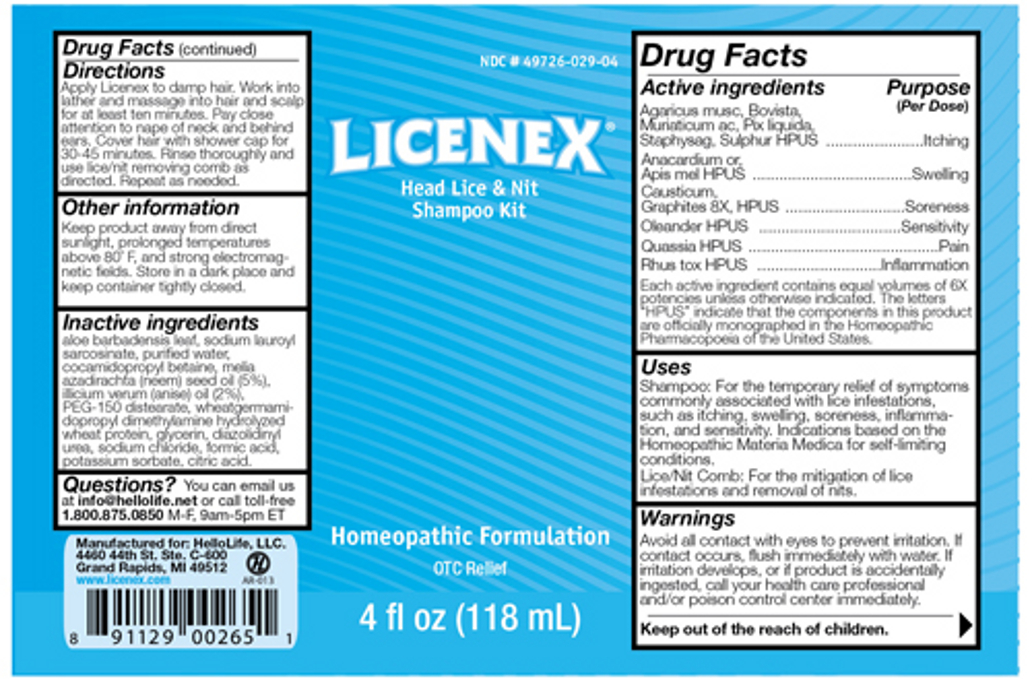 DRUG LABEL: Licenex
NDC: 49726-029 | Form: SHAMPOO
Manufacturer: Hello Life, Inc.
Category: homeopathic | Type: HUMAN OTC DRUG LABEL
Date: 20181226

ACTIVE INGREDIENTS: AMANITA MUSCARIA FRUITING BODY 6 [hp_X]/118 mL; LYCOPERDON UTRIFORME FRUITING BODY 6 [hp_X]/118 mL; HYDROCHLORIC ACID 6 [hp_X]/118 mL; QUASSIA AMARA WOOD 6 [hp_X]/118 mL; PINE TAR 6 [hp_X]/118 mL; DELPHINIUM STAPHISAGRIA SEED 6 [hp_X]/118 mL; SULFUR 6 [hp_X]/118 mL; SEMECARPUS ANACARDIUM JUICE 6 [hp_X]/118 mL; APIS MELLIFERA 6 [hp_X]/118 mL; CAUSTICUM 6 [hp_X]/118 mL; GRAPHITE 8 [hp_X]/118 mL; NERIUM OLEANDER LEAF 6 [hp_X]/118 mL; TOXICODENDRON PUBESCENS LEAF 6 [hp_X]/118 mL
INACTIVE INGREDIENTS: ALOE VERA LEAF; AZADIRACHTA INDICA SEED OIL; WATER; SODIUM LAUROYL SARCOSINATE; COCAMIDOPROPYL BETAINE; GLYCERIN; STAR ANISE OIL; PEG-150 DISTEARATE; DIAZOLIDINYL UREA; CITRIC ACID MONOHYDRATE; SODIUM CHLORIDE; FORMIC ACID; POTASSIUM SORBATE

Active Ingredients

Agaricus musc, Bovista, Muriaticum ac, Pix liquida, Staphysag, Sulphur HPUS

Anacardium or, Apis mel HPUS

Causticum, Graphites 8X HPUS

Oleander HPUS

Rhus tox HPUS

Each active ingredient contains equal volumes of 6X potencies unless otherwise indicated. The letters "HPUS" indicate that the components in this product are officially monographed in the Homeopathic Pharmacopoeia of the United States.

Purpose

Agaricus musc, Bovista, Muriaticum ac, Pix liquida, Staphysag, Sulphur HPUS........................Itching

Anacardium or, Apis mel HPUS...........................................................................................Swelling

Causticum, Graphites 8X HPUS.........................................................................................Soreness

Oleander HPUS.............................................................................................................. Sensitivity

Rhus tox HPUS...........................................................................................................Inflammation

Uses

Shampoo: For the temporary relief of symptoms commonly associated with lice infestations, such as itching, swelling, soreness, inflammation, and sensitivity. Indications based on the Homeopathic Materia Medica for self-limiting conditions.

Lice/Nit Comb: For the mitigation of lice infestations and removal of nits.

Warnings

Avoid all contact with the eyes to prevent irritation. If contact occurs, flush immediately with water. If irritation develops, or if product is accidentally ingested, call your health care professional and/or poison control center immediately.

Keep out of the reach of children.

Directions

Apply Licenex to damp hair. Work into lather and massage into hair and scalp for at least ten minutes. Pay close attention to nape of neck and behind ears. Cover hair with shower cap for 30-45 minutes. Rinse thoroughly and use lice/nit removing comb as directed. Repeat as needed.

Other Information

Keep product away from direct sunlight, prolonged temperatures above 80 degrees F, and strong electromagnetic fields. Store in a dark place and keep container tightly closed.

Inactive ingredients

aloe barbadensis leaf, sodium lauroyl sarcosinate, purified water, cocamidopropyl betaine, melia illicium verum (anise) oil (2%), PEG-150 distearate, wheatgermamidopropyl dimethylamine hydrolyzed wheat protein, glycerin, diazolidinyl urea, sodium chloride, formic acid, potassium sorbate, citric acid

Questions

You can email us at info@hellolife.net or call toll-free 1.800.875.0850 M-F, 9am-5pm ET.

DESCRIPTION

Manufactured for: HelloLife, LLC.
4460 44th St. Ste. C-600
Grand Rapids, MI 49512

www.licenex.com

Principal Display Panel

NDC #49726-029-04

LICENEX

Head Lice and Nit Shampoo Kit

Homeopathic Formulation
OTC Relief

4 fl oz (118 mL)